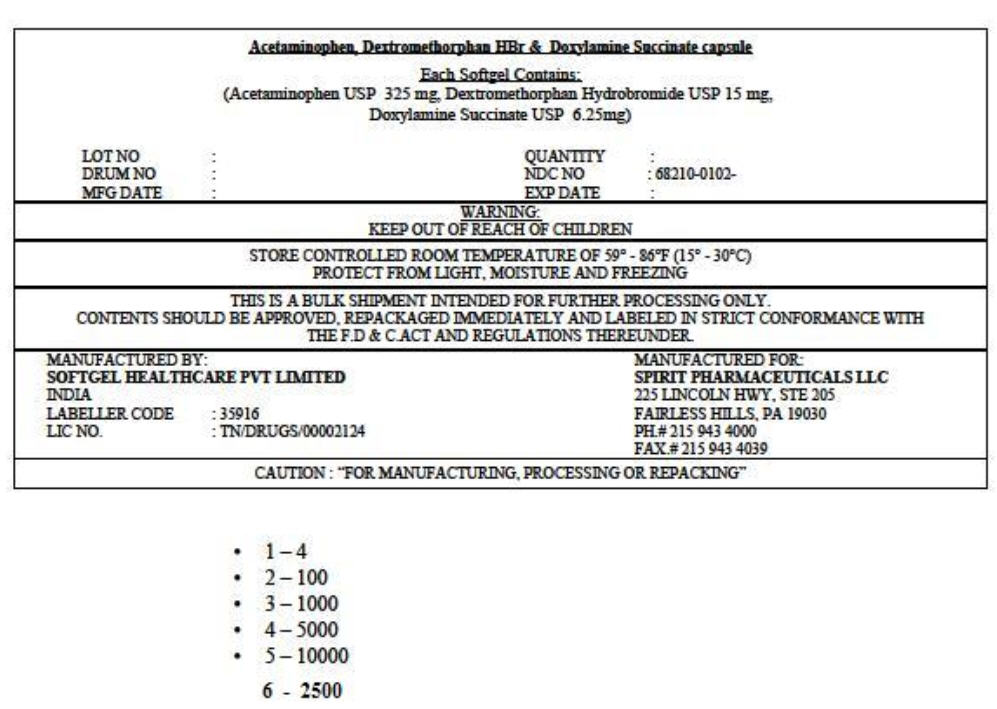 DRUG LABEL: ACETAMINOPHEN, DEXTROMETHORPHAN HYDROBROMIDE, and DOXYLAMINE SUCCINATE
NDC: 68210-0102 | Form: CAPSULE, LIQUID FILLED
Manufacturer: SPIRIT PHARMACEUTICALS, LLC
Category: otc | Type: HUMAN OTC DRUG LABEL
Date: 20100901

ACTIVE INGREDIENTS: ACETAMINOPHEN 325 mg/1 1; DEXTROMETHORPHAN HYDROBROMIDE 15 mg/1 1; DOXYLAMINE SUCCINATE 6.25 mg/1 1
INACTIVE INGREDIENTS: POLYETHYLENE GLYCOL 400; POLYETHYLENE GLYCOL 600; GELATIN; POVIDONE; SORBITOL; WATER; BUTYLATED HYDROXYANISOLE; BUTYLATED HYDROXYTOLUENE

Acetaminophen, Dextromethorpan HBr & Doxylamine Succinate capsule

Drug Facts

ACTIVE INGREDIENT

Active ingredients (in each LiquiCap) | Purpose
Acetaminophen 325 mg | Pain reliever/fever reducer
Dextromethorphan HBr 15 mg | Cough suppressant
Doxylamine succinate 6.25 mg | Antihistamine

Uses

temporarily relieves common cold/flu symptoms:

- cough due to minor throat and bronchial irritation
- sore throat
- headache
- minor aches and pains
- fever
- runny nose and sneezing

Warnings

Alcohol warning: If you consume 3 or more alcoholic drinks every day, ask your doctor whether you should take acetaminophen or other pain relievers/fever reducers. Acetaminophen may cause liver damage.

Sore throat warning: If sore throat is severe, persists for more than two days, is accompanied or followed by fever, headache, rash, nausea, or vomiting, consult a doctor promptly.

Do not use

- with other medicines containing acetaminophen
- if you are now taking a prescription monoamine oxidase inhibitor (MAOI) (certain drugs for depression, psychiatric or emotional conditions, or Parkinson's disease), or for 2 weeks after stopping the MAOI drug. If you do not know if your prescription drug contains an MAOI, ask a doctor or pharmacist before taking this product.

Ask a doctor before use if you have

- glaucoma
- cough that occurs with too much phlegm (mucus)
- a breathing problem or chronic cough that lasts or as occurs with smoking, asthma, chronic bronchitis or emphysema
- trouble urinating due to enlarged prostate gland

Ask a doctor or pharmacist before use if you are taking sedatives or tranquilizers.

When using this product

- do not use more than directed
- excitability may occur, especially in children
- marked drowsiness may occur
- avoid alcoholic drinks
- be careful when driving a motor vehicle or operating machinery
- alcohol, sedatives, and tranquilizers may increase drowsiness

Stop use and ask a doctor if

- pain or cough gets worse or lasts more than 7 days
- fever gets worse or lasts more than 3 days
- redness or swelling is present
- new symptoms occur
- cough comes back or occurs with rash or headache that lasts.

These could be signs of a serious condition.

PREGNANCY OR BREAST FEEDING

If pregnant or breast-feeding, ask a health professional before use.

Keep out of reach of children.

OVERDOSAGE

Overdose warning: Taking more than the recommended dose can cause serious health problems. In case of overdose, get medical help or contact a Poison Control Center right away. Quick medical attention is critical for adults as well as for children even if you do not notice any signs or symptoms.

Directions

- take only as recommended - see Overdose warning
- do not exceed 4 doses per 24 hours

adults and children 12 years and over | 2 LiquiCaps with water every 6 hours
children under 12 years | ask a doctor

- when using other DayQuil or NyQuil products, carefully read each label to insure correct dosing

Other information

- store at room temperature

Inactive ingredients

D&C Yellow No. 10, FD&C Blue No. 1, gelatin, glycerin, polyethylene glycol, povidone, propylene glycol, purified water, sorbitol special, titanium dioxide

PRINCIPAL DISPLAY PANEL

Acetaminophen, Dextromethorphan HBr & Doxylamine Succinate capsule

Each Softgel Contains:
(Acetaminophen USP 325 mg, Dextromethorphan Hydrobromide USP 15 mg,
Doxylamine Succinate USP 6.25mg)

LOT NO:
DRUM NO:
MFG DATE:
QUANTITY:
NDC NO: 68210-0102-
EXP DATE:

WARNING:
KEEP OUT OF REACH OF CHILDREN

STORE CONTROLLED ROOM TEMPERATURE OF 59° - 86°F (15° - 30°C)
PROTECT FROM LIGHT, MOISTURE AND FREEZING

THIS IS A BULK SHIPMENT INTENDED FOR FURTHER PROCESSING ONLY.
CONTENTS SHOULD BE APPROVED, REPACKAGED IMMEDIATELY AND LABELED IN STRICT CONFORMANCE WITH
THE F.D & C.ACT AND REGULATIONS THEREUNDER.

MANUFACTURED BY:
SOFTGEL HEALTHCARE PVT LIMITED
INDIA
LABELLER CODE: 35916
LIC NO.: TN/DRUGS/00002124

MANUFACTURED FOR:
SPIRIT PHARMACEUTICALS LLC
225 LINCOLN HWY, STE 205
FAIRLESS HILLS, PA 19030
PH.# 215 943 4000
FAX.# 215 943 4039

CAUTION: "FOR MANUFACTURING, PROCESSING OR REPACKING"

- 1 – 4
- 2 – 100
- 3 – 1000
- 4 – 5000
- 5 – 10000
  6 - 2500